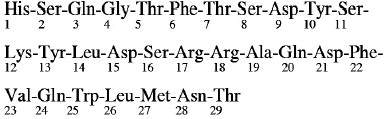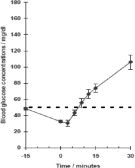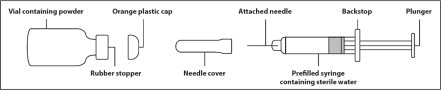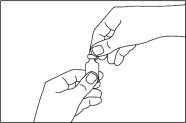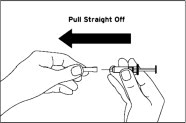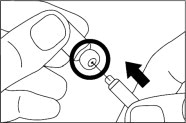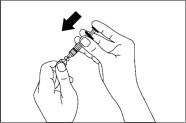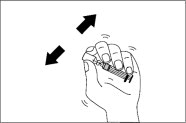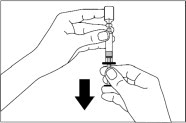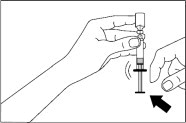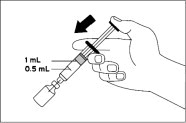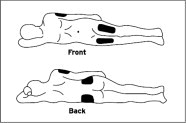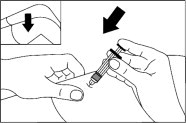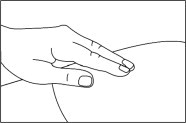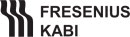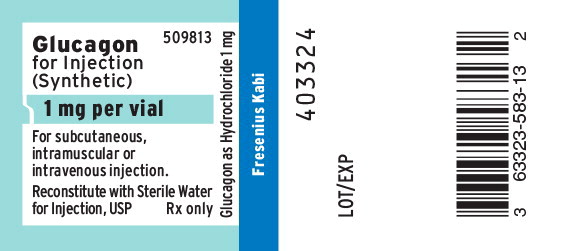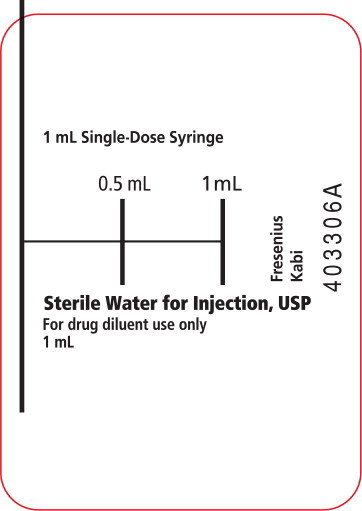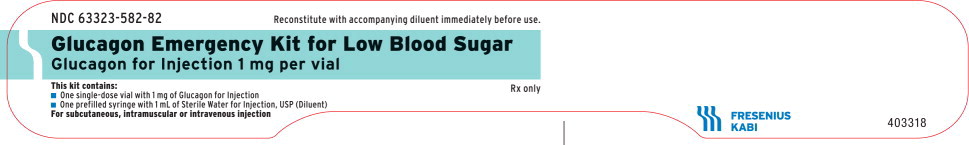 DRUG LABEL: Glucagon

NDC: 63323-582 | Form: KIT | Route: INTRAMUSCULAR
Manufacturer: Fresenius Kabi USA, LLC
Category: prescription | Type: HUMAN PRESCRIPTION DRUG LABEL
Date: 20250331

ACTIVE INGREDIENTS: GLUCAGON HYDROCHLORIDE
 1 mg/1 mL; WATER
 1 mL/1 mL
INACTIVE INGREDIENTS: LACTOSE MONOHYDRATE; HYDROCHLORIC ACID; SODIUM HYDROXIDE

HIGHLIGHTS OF PRESCRIBING INFORMATION

These highlights do not include all the information needed to use GLUCAGON FOR INJECTION safely and effectively. See full prescribing information for GLUCAGON FOR INJECTION.
GLUCAGON for injection, for subcutaneous, intramuscular or intravenous use
Initial U.S. Approval: 1960

RECENT MAJOR CHANGES

Indications and Usage (1) | 09/2019
Dosage and Administration (2) | 09/2019
Contraindications (4) | 09/2019
Warnings and Precautions (5) | 09/2019

1 INDICATIONS AND USAGE

Glucagon for Injection is an antihypoglycemic agent and a gastrointestinal motility inhibitor indicated:

- for the treatment of severe hypoglycemia in pediatric and adult patients with diabetes (1.1)
- as a diagnostic aid for use during radiologic examinations to temporarily inhibit movement of the gastrointestinal tract in adult patients (1.2)

2 DOSAGE AND ADMINISTRATION

Dosage in adults and pediatric patients using the glucagon emergency kit for low blood sugar to treat severe hypoglycemia (2.2)

- Adults and Pediatric Patients Weighing More Than 25 kg or for Pediatric Patients with Unknown Weight 6 Years and Older:
  - The recommended dosage is 1 mg (1 mL) injected subcutaneously or intramuscularly into the upper arm, thigh, or buttocks, or intravenously.
  - If there has been no response after 15 minutes, an additional 1 mg dose (1 mL) of Glucagon for Injection may be administered using a new kit while waiting for emergency assistance.
- Pediatric Patients Weighing Less Than 25 kg or for Pediatric Patients with Unknown Weight Less Than 6 Years of Age:
  - The recommended dosage is 0.5 mg (0.5 mL) injected subcutaneously or intramuscularly into the upper arm, thigh, or buttocks, or intravenously.
  - If there has been no response after 15 minutes, an additional 0.5 mg dose (0.5 mL) of Glucagon for Injection may be administered using a new kit while waiting for emergency assistance.

Important Administration Instructions for Using the Glucagon Emergency Kit for Low Blood Sugar to Treat

Severe Hypoglycemia (2.1)

- Glucagon for Injection is for subcutaneous, intramuscular, or intravenous injection. Administer intravenously ONLY under medical supervision.
- See the Full Prescribing Information for administration instructions

Dosage in Adults for Using Glucagon for Injection Diagnostic Kit and Glucagon for Injection Single-Dose Vial as a Diagnostic Aid (2.4)

- The recommended diagnostic dose for relaxation of the stomach, duodenal bulb, duodenum, and small bowel is 0.2 mg to 0.5 mg administered intravenously or 1 mg administered intramuscularly; the recommended dose to relax the colon is 0.5 mg to 0.75 mg administered intravenously or 1 mg to 2 mg administered intramuscularly.
- See the Full Prescribing Information for administration instructions (2.3)

3 DOSAGE FORMS AND STRENGTHS

For Injection (3):

- Treatment of Severe Hypoglycemia: 1 mg single-dose vial of Glucagon for Injection with a 1 mL single-dose syringe of Sterile Water for Injection, USP (Glucagon Emergency Kit for Low Blood Sugar)
- Use as a Diagnostic Aid: 1 mg single-dose vial of Glucagon for Injection
- Use as a Diagnostic Aid: 1 mg single-dose vial of Glucagon for Injection with a 1 mL single-dose vial of Sterile Water for Injection, USP (Diagnostic Kit)

4 CONTRAINDICATIONS

- Pheochromocytoma (4)
- Insulinoma (4)
- Known hypersensitivity to glucagon or to any of the excipients (4)
- Glucagonoma when used as a diagnostic aid (4)

5 WARNINGS AND PRECAUTIONS

- Catecholamine Release in Patients with Pheochromocytoma: Contraindicated in patients with pheochromocytoma because Glucagon for Injection may stimulate the release of catecholamines from the tumor. (4, 5.1)
- Hypoglycemia in Patients with Insulinoma: In patients with insulinoma, administration may produce an initial increase in blood glucose; however, Glucagon for Injection may stimulate exaggerated insulin release from an insulinoma and cause hypoglycemia. If a patient develops symptoms of hypoglycemia after a dose of Glucagon for Injection, give glucose orally or intravenously. (4, 5.2)
- Hypersensitivity and Allergic Reactions: Allergic reactions have been reported and include generalized rash, and in some cases anaphylactic shock with breathing difficulties, and hypotension. (4, 5.3)
- Lack of Efficacy in Patients with Decreased Hepatic Glycogen: Glucagon for Injection is effective in treating hypoglycemia only if sufficient hepatic glycogen is present. Patients in states of starvation, with adrenal insufficiency or chronic hypoglycemia may not have adequate levels of hepatic glycogen for Glucagon for Injection to be effective. Patients with these conditions should be treated with glucose. (5.4)
- Necrolytic Migratory Erythema (NME): a skin rash, has been reported postmarketing following continuous glucagon infusion and resolved with discontinuation of the glucagon. Should NME occur, consider whether the benefits of continuous glucagon infusion outweigh the risks. (5.5)
- Hyperglycemia in Patients with Diabetes Mellitus when Used as a Diagnostic Aid: Treatment with Glucagon for Injection in patients with diabetes mellitus may cause hyperglycemia. Monitor diabetic patients for changes in blood glucose levels during treatment and treat if indicated.(5.6)
- Blood Pressure and Heart Rate Increase in Patients with Cardiac Disease when Used as a Diagnostic Aid: Glucagon for Injection may increase myocardial oxygen demand, blood pressure, and pulse rate. Cardiac monitoring is recommended in patients with cardiac disease during use of Glucagon for Injection as a diagnostic aid, and an increase in blood pressure and pulse rate may require therapy. (5.7)
- Hypoglycemia in Patients with Glucagonoma when Used as a Diagnostic Aid: Glucagon administered to patients with glucagonoma may cause secondary hypoglycemia. Test patients suspected of having glucagonoma for blood levels of glucagon prior to treatment, and monitor blood glucose levels during treatment. If a patient develops hypoglycemia, give glucose orally or intravenously. (5.8)

6 ADVERSE REACTIONS

Most common adverse reactions (>5% or greater incidence): Injection site swelling, injection site erythema, vomiting, nausea, decreased blood pressure, asthenia, headache, dizziness, pallor, diarrhea, and somnolence.

To report SUSPECTED ADVERSE REACTIONS, contact Fresenius Kabi USA, LLC at 1-800-551-7176 or FDA at 1-800-FDA-1088 or www.fda.gov/medwatch.

7 DRUG INTERACTIONS

- Beta-blockers: Patients taking beta-blockers may have a transient increase in pulse and blood pressure. (7.1)
- Indomethacin: In patients taking indomethacin Glucagon for Injection may lose its ability to raise glucose or may produce hypoglycemia. (7.2)
- Anticholinergic drugs: Concomitant use of anticholinergic drugs with Glucagon for Injection for use as a diagnostic aid is not recommended. (7.3)
- Warfarin: Glucagon for Injection may increase the anticoagulant effect of warfarin. (7.4)
- Insulin: Monitor blood glucose when Glucagon for Injection is used as a diagnostic aid in patients receiving insulin. (7.5)

FULL PRESCRIBING INFORMATION

1 INDICATIONS AND USAGE

1.1 Severe Hypoglycemia

Glucagon for Injection is indicated for the treatment of severe hypoglycemia in pediatric and adult patients with diabetes.

1.2 Diagnostic Aid

Glucagon for Injection is indicated as a diagnostic aid for use during radiologic examinations to temporarily inhibit movement of the gastrointestinal tract in adult patients.

2 DOSAGE AND ADMINISTRATION

2.1 Important Administration Instructions for Using the Glucagon Emergency Kit for Low Blood Sugar to Treat Severe Hypoglycemia

Glucagon for Injection is for subcutaneous, intramuscular, or intravenous injection. Administer intravenously ONLY under medical supervision.

Instruct patients and their caregivers on the signs and symptoms of severe hypoglycemia. Because severe hypoglycemia requires the help of others to recover, instruct the patient to inform those around them about Glucagon for Injection and its Instructions for Use. Administer Glucagon for Injection as soon as possible when severe hypoglycemia is recognized.

Instruct the patient or caregiver to read the Instructions for Use at the time they receive a prescription for Glucagon for Injection. Emphasize the following instructions to the patient or caregiver:

- Using the supplied prefilled syringe, carefully insert the needle through the rubber stopper of the vial containing Glucagon for Injection powder and inject all the liquid from the syringe into the vial.
- Shake the vial gently until the powder is completely dissolved and no particles remain in the fluid. The reconstituted solution should be clear and colorless. Inspect visually for particulate matter and discoloration. If the resulting solution is cloudy or contains particulate matter do not use.
- The reconstituted solution is 1 mg per mL glucagon.
- Immediately after reconstitution, inject the solution subcutaneously or intramuscularly in the upper arm, thigh, or buttocks. In addition, healthcare providers may administer intravenously.
- Call for emergency assistance immediately after administering the dose.
- When the patient has responded to the treatment and is able to swallow, give oral carbohydrates to restore the liver glycogen and prevent recurrence of hypoglycemia.
- Discard any unused portion.

2.2 Dosage in Adults and Pediatric Patients for Using the Glucagon Emergency Kit for Low Blood Sugar to Treat Severe Hypoglycemia

Adults and Pediatric Patients Weighing More Than 25 kg or for Pediatric Patients with Unknown Weight 6 Years and Older

- The recommended dosage is 1 mg (1 mL) injected subcutaneously or intramuscularly into the upper arm, thigh, or buttocks, or intravenously.
- If there has been no response after 15 minutes, an additional 1 mg dose (1 mL) of Glucagon for Injection may be administered using a new kit while waiting for emergency assistance.

Pediatric Patients Weighing Less Than 25 kg or for Pediatric Patients with Unknown Weight Less Than 6 Years of Age

- The recommended dosage is 0.5 mg (0.5 mL) injected subcutaneously or intramuscularly into the upper arm, thigh, or buttocks, or intravenously.
- If there has been no response after 15 minutes, an additional 0.5 mg dose (0.5 mL) of Glucagon for Injection may be administered using a new kit while waiting for emergency assistance.

2.3 Important Administration Instruction for Using Glucagon for Injection Diagnostic Kit and Glucagon for Injection Single-Dose Vial as a Diagnostic Aid

- Reconstitute Glucagon for Injection with 1 mL of Sterile Water for Injection. Using a syringe, withdraw all of the Sterile Water for Injection (if supplied) or 1 mL Sterile Water for Injection and inject into the Glucagon for Injection vial.
- Shake the vial gently until the powder is completely dissolved and no particles remain in the fluid. The reconstituted fluid should be clear and colorless. Inspect visually for particulate matter and discoloration. If the resulting solution is cloudy or contains particulate matter do not use.
- The reconstituted solution is 1 mg per mL glucagon.
- Immediately after reconstitution, inject the solution intravenously or intramuscularly into upper arm, thigh, or buttocks.
- Discard any unused portion.
- After the end of the diagnostic procedure, give oral carbohydrates to patients who have been fasting, if this is compatible with the diagnostic procedure.

2.4 Dosage in Adults for Using Glucagon for Injection Diagnostic Kit and Glucagon for Injection Single-Dose Vial as a Diagnostic Aid

- The recommended diagnostic dose for relaxation of the stomach, duodenal bulb, duodenum, and small bowel is 0.2 mg to 0.5 mg administered intravenously or 1 mg administered intramuscularly; the recommended dose to relax the colon is 0.5 mg to 0.75 mg administered intravenously or 1 mg to 2 mg administered intramuscularly [see Clinical Pharmacology (12.2)].
- The onset of action after an injection will depend on the organ under examination and route of administration [see Clinical Pharmacology (12.2)].

3 DOSAGE FORMS AND STRENGTHS

Glucagon for Injection is a white lyophilized powder supplied as follows:

Treatment of Severe Hypoglycemia

- 1 mg single-dose vial of Glucagon for Injection with a 1 mL single-dose syringe of Sterile Water for Injection, USP (Glucagon Emergency Kit for Low Blood Sugar)

Use as a Diagnostic Aid

- 1 mg single-dose vial of Glucagon for Injection
- 1 mg single-dose vial of Glucagon for Injection with a 1 mL single-dose vial of Sterile Water for Injection, USP (Diagnostic Kit)

4 CONTRAINDICATIONS

Glucagon for Injection is contraindicated in patients with:

- Pheochromocytoma [see Warnings and Precautions (5.1)]
- Insulinoma [see Warnings and Precautions (5.2)] because of the risk of hypoglycemia
- Known hypersensitivity to glucagon or any of the excipients in Glucagon for Injection. Allergic reactions have been reported with glucagon and include anaphylactic shock with breathing difficulties and hypotension [see Warnings and Precautions (5.3)]
- Glucagonoma [see Warnings and Precautions (5.8)] because of risk of hypoglycemia when used as a diagnostic aid

5 WARNINGS AND PRECAUTIONS

5.1 Catecholamine Release in Patients with Pheochromocytoma

Glucagon for Injection is contraindicated in patients with pheochromocytoma because glucagon may stimulate the release of catecholamines from the tumor [see Contraindications (4)]. If the patient develops a dramatic increase in blood pressure and a previously undiagnosed pheochromocytoma is suspected, 5 to 10 mg of phentolamine mesylate, administered intravenously, has been shown to be effective in lowering blood pressure.

5.2 Hypoglycemia in Patients with Insulinoma

In patients with insulinoma, administration of glucagon may produce an initial increase in blood glucose; however, Glucagon for Injection administration may directly or indirectly (through an initial rise in blood glucose) stimulate exaggerated insulin release from an insulinoma and cause hypoglycemia. Glucagon for Injection is contraindicated in patients with insulinoma [see Contraindications (4)]. If a patient develops symptoms of hypoglycemia after a dose of Glucagon for Injection, give glucose orally or intravenously.

5.3 Hypersensitivity and Allergic Reactions

Allergic reactions have been reported with glucagon, these include generalized rash, and in some cases anaphylactic shock with breathing difficulties and hypotension. Glucagon for Injection is contraindicated in patients with a prior hypersensitivity reaction [see Contraindications (4)].

5.4 Lack of Efficacy in Patients with Decreased Hepatic Glycogen

Glucagon for Injection is effective in treating hypoglycemia only if sufficient hepatic glycogen is present. Patients in states of starvation, with adrenal insufficiency or chronic hypoglycemia may not have adequate levels of hepatic glycogen for Glucagon for Injection administration to be effective. Patients with these conditions should be treated with glucose.

5.5 Necrolytic Migratory Erythema

Necrolytic migratory erythema (NME), a skin rash commonly associated with glucagonomas (glucagonproducing tumors) and characterized by scaly, pruritic erythematous plaques, bullae, and erosions, has been reported postmarketing following continuous glucagon infusion. NME lesions may affect the face, groin, perineum and legs or be more widespread. In the reported cases NME resolved with discontinuation of the glucagon, and treatment with corticosteroids was not effective. Should NME occur, consider whether the benefits of continuous glucagon infusion outweigh the risks.

5.6 Hyperglycemia in Patients with Diabetes Mellitus when Used as a Diagnostic Aid

Treatment with Glucagon for Injection in patients with diabetes mellitus may cause hyperglycemia. Monitor diabetic patients for changes in blood glucose levels during treatment and treat if indicated.

5.7 Blood Pressure and Heart Rate Increase in Patients with Cardiac Disease when Used as a Diagnostic Aid

Glucagon for Injection may increase myocardial oxygen demand, blood pressure, and pulse rate which may be life-threatening in patients with cardiac disease. Cardiac monitoring is recommended in patients with cardiac disease during use of Glucagon for Injection as a diagnostic aid, and an increase in blood pressure and pulse rate may require therapy.

5.8 Hypoglycemia in Patients with Glucagonoma

Glucagon administered to patients with glucagonoma may cause secondary hypoglycemia. Glucagon for Injection is contraindicated in patients with glucagonoma when used as a diagnostic aid [see Contraindications (4)]. Test patients suspected of having glucagonoma for blood levels of glucagon prior to treatment, and monitor for changes in blood glucose levels during treatment. If a patient develops symptoms of hypoglycemia after a dose of Glucagon for Injection, give glucose orally or intravenously.

6 ADVERSE REACTIONS

The following important adverse reactions are described below and elsewhere in the labeling:

- Hypersensitivity and Allergic Reactions [see Warnings and Precautions (5.3)]
- Necrolytic Migratory Erythema [see Warnings and Precautions (5.5)]
- Hyperglycemia in Patients with Diabetes Mellitus when Used as a Diagnostic Aid [see Warnings and Precautions (5.6)]
- Blood Pressure and Heart Rate Increase in Patients with Cardiac Disease when Used as a Diagnostic Aid [see Warnings and Precautions (5.7)]

6.1 Clinical Studies Experience

Because clinical trials are conducted under widely varying conditions, adverse reaction rates observed in the clinical trials of a drug cannot be directly compared to the rates in clinical trials of another drug and may not reflect the rates observed in practice.

In a randomized single-blind clinical study of Glucagon for Injection, 29 healthy subjects received a single dose of 1 mg Glucagon for Injection intramuscularly. Table 1 shows the most common adverse reactions that were not present at baseline and occurred in at least 5% of patients.

Table 1: Adverse Reactions Occurring in ≥ 5% of Healthy Subjects Who Received Glucagon for Injection Intramuscularly
 | Glucagon for Injection (N=29) % of Patients
Nausea | 17
Vomiting | 7

In a randomized, single-blind clinical study of Glucagon for Injection, 31 healthy subjects received a single dose of 1 mg Glucagon for Injection subcutaneously. Table 2 shows the most common adverse reactions that were not present at baseline and occurred in at least 5% of patients. (2.1)].

Table 2: Adverse Reactions Occurring ≥5% in Healthy Subjects Who Received Glucagon for Injection Subcutaneously
 | Glucagon for Injection (N=31) % of Patients
Injection site swelling | 58
Injection site erythema | 55
Vomiting | 36
Nausea | 32
Decreased blood pressure | 23
Asthenia | 23
Headache | 13
Dizziness | 10
Pallor | 10
Diarrhea | 7
Somnolence | 7

Other Adverse Reactions

Hypertension and tachycardia have occurred with glucagon treatment.

6.2 Postmarketing Experience

Additional adverse reactions have been identified during post-approval use of glucagon. Because these reactions are reported voluntarily from a population of uncertain size, it is generally not possible to reliably estimate their frequency or establish a causal relationship to drug exposure.

- hypoglycemia and hypoglycemic coma. Patients taking indomethacin may be more likely to experience hypoglycemia following glucagon administration [see Drug Interactions (7)].
- Necrolytic migratory erythema (NME) cases have been reported postmarketing in patients receiving continuous infusion of glucagon.

7 DRUG INTERACTIONS

7.1

Table 3: Clinically Significant Drug Interactions with Glucagon for Injection
Beta-Blockers
Clinical Impact: | Patients taking beta-blockers may have a transient increase in pulse and blood pressure when given Glucagon for Injection.
Intervention: | The increase in blood pressure and heart rate may require therapy in patients with coronary artery disease.
Indomethacin
Clinical Impact: | In patients taking indomethacin, Glucagon for Injection may lose its ability to raise blood glucose or may even produce hypoglycemia.
Intervention: | Monitor blood glucose levels during glucagon treatment of patients taking indomethacin.
Anticholinergic Drugs
Clinical Impact: | The concomitant use of anticholinergic drugs and Glucagon for Injection increases the risk of gastrointestinal adverse reactions due to additive effects on inhibition of gastrointestinal motility.
Intervention: | Concomitant use of anticholinergic drugs with Glucagon for Injection for use as a diagnostic aid is not recommended.
Warfarin
Clinical Impact: | Glucagon for Injection may increase the anticoagulant effect of warfarin.
Intervention: | Monitor patients for unusual bruising or bleeding, as adjustments in warfarin dosage may be required.
Insulin
Clinical Impact: | Insulin acts antagonistically to glucagon.
Intervention: | Monitor blood glucose when Glucagon for Injection is used as a diagnostic aid in patients receiving insulin.

8 USE IN SPECIFIC POPULATIONS

8.1 Pregnancy

Risk Summary

Available data from case reports and a small number of observational studies with glucagon use in pregnant women over decades of use have not identified a drug-associated risk of major birth defects, miscarriage or adverse maternal or fetal outcomes. Multiple small studies have demonstrated a lack of transfer of pancreatic glucagon across the human placental barrier during early gestation. In rat and rabbit reproduction studies, no embryofetal toxicity was observed with glucagon administered by injection during the period of organogenesis at doses representing up to 100 and 200 times the human dose, respectively, based on body surface area (mg/m^2) (see Data).

The estimated background risk of major birth defects and miscarriage for the indicated population is unknown. In the U.S. general population, the estimated background risk of major birth defects and miscarriage in clinically recognized pregnancies is 2%-4% and 15%-20%, respectively.

Data

Animal Data

In rats and rabbits given glucagon by injection at doses of 0.4, 2.0, and 10 mg/kg (up to 100 and 200 times the human dose based on mg/m^2 for rats and rabbits, respectively) there was no evidence of increased malformations or embryofetal lethality.

8.2 Lactation

Risk Summary

There is no information available on the presence of glucagon in human or animal milk, the effects of glucagon on the breastfed child or the effects of glucagon on milk production. However, glucagon is a peptide and would be expected to be broken down to its constituent amino acids in the infant's digestive tract and is therefore, unlikely to cause harm to an exposed infant.

8.4 Pediatric Use

The safety and effectiveness of Glucagon for Injection for the treatment of severe hypoglycemia in pediatric patients with diabetes have been established.

Safety and effectiveness for use as a diagnostic aid during radiologic examinations to temporarily inhibit movement of the gastrointestinal tract in pediatric patients have not been established.

10 OVERDOSAGE

If overdosage occurs, the patient may experience nausea, vomiting, inhibition of GI tract motility, increase in blood pressure and pulse rate. In case of suspected overdosing, the serum potassium may decrease and should be monitored and corrected if needed. If the patient develops a dramatic increase in blood pressure, phentolamine mesylate has been shown to be effective in lowering blood pressure for the short time that control would be needed.

11 DESCRIPTION

Glucagon is an antihypoglycemic agent and a gastrointestinal motility inhibitor. It is produced by solid phase peptide synthesis. The chemical structure of the glucagon is identical to human glucagon. Glucagon is a single-chain polypeptide containing 29 amino acid residues. The structure of glucagon is:

Molecular Formula = C153H225N43O49S

Molecular Weight = 3483

Glucagon for Injection is a sterile, lyophilized white powder in a 3 mL vial for subcutaneous, intramuscular or intravenous use. The reconstituted solution contains glucagon as hydrochloride 1 mg per mL and lactose monohydrate (107 mg). Glucagon for Injection is supplied at pH 2.5 to 3.5 and is soluble in water.

12 CLINICAL PHARMACOLOGY

12.1 Mechanism of Action

Glucagon increases blood glucose concentration by activating hepatic glucagon receptors, thereby stimulating glycogen breakdown and release of glucose from the liver. Hepatic stores of glycogen are necessary for glucagon to produce an antihypoglycemic effect. Extrahepatic effects of glucagon include relaxation of the smooth muscle of the stomach, duodenum, small bowel, and colon.

12.2 Pharmacodynamics

Treatment of Severe Hypoglycemia

Blood glucose concentration rises within 10 minutes of injection and maximal concentrations are attained at approximately 30 minutes after injection (see Figure 1). The duration of hyperglycemic action after intravenous or intramuscular injection is 60 to 90 minutes.

Figure 1. Recovery from Insulin Induced Hypoglycemia (mean blood glucose) After Intramuscular Injection of 1 mg of Another Glucagon for Injection Product in Type I Diabetic Men

Diagnostic Aid

Table 4: Pharmacodynamic Properties of Another Glucagon for Injection Product For Intravenous Route
Route of Administration | Dosea | Time of Maximal Glucose Concentration | Time of Onset of Action for GI Smooth Muscle Relaxation | Duration of Smooth Muscle Relaxation
Intravenous | 0.25 to 0.5 mg | 5 to 20 minutes | 45 seconds | 9 to 17 minutes
aDose is determined based on the length of the procedure.

Table 5 Pharmacodynamic Properties of Another Glucagon for Injection Product For Intramuscular Route
Route of Administration | Dosea | Time of Maximal Glucose Concentration | Time of Onset of Action for GI Smooth Muscle Relaxation | Duration of Smooth Muscle Relaxation
Intramuscular | 1 mg | 30 minutes | 8 to 10 minutes | 12 to 27 minutes
Intramuscular | 2 mg | 30 minutes | 4 to 7 minutes | 21 to 32 minutes
aDose is determined based on the length of the procedure.

In a study in healthy subjects, a subcutaneous dose of 1 mg Glucagon for Injection resulted on average a peak blood glucose concentration of 79.3 mg/dL with a median time of 50 minutes after injection.

12.3 Pharmacokinetics

Absorption

Following subcutaneous administration of Glucagon for Injection, the median time to reach the maximum baseline uncorrected plasma glucagon concentrations of 3533 pg/mL was approximately 10 to 13 minutes after dosing Following intramuscular administration of 1 mg dose, the maximum baseline uncorrected plasma glucagon concentrations of 3391 pg/mL were attained approximately 10 minutes after dosing.

Elimination

The mean apparent half-life of glucagon was about 42 minutes after subcutaneous administration. The mean apparent half-life of glucagon was 26 minutes after intramuscular administration.

Metabolism

Glucagon is degraded in the liver, kidney, and plasma.

13 NONCLINICAL TOXICOLOGY

13.1 Carcinogenesis, Mutagenesis, Impairment of Fertility

Carcinogenesis

Long term studies in animals to evaluate carcinogenic potential have not been performed.

Mutagenesis

Synthetic glucagon was negative in the bacterial reverse mutation assay (Ames test). The clastogenic potential of synthetic glucagon in the Chinese Hamster Ovary (CHO) assay was positive in the absence of metabolic activation. Doses of 100 and 200 mg/kg of glucagon of both pancreatic and recombinant origins gave slightly higher incidences of micronucleus formation in male mice but there was no effect in females. The weight of evidence indicates that synthetic and recombinant glucagon are not different and do not pose a genotoxic risk to humans.

Impairment of Fertility

Glucagon was not tested in animal fertility studies. Studies in rats have shown that pancreatic glucagon does not cause impaired fertility.

16 HOW SUPPLIED/STORAGE AND HANDLING

16.1 How Supplied

Glucagon for Injection is supplied as a sterile, lyophilized white powder available as follows:

Presentation | NDC | Strength | Description
Treatment of Severe Hypoglycemia
Glucagon Emergency Kit for Low Blood Sugar | 63323-582-82 | 1 mg per vial | 1 mL single-dose vial of Glucagon for Injection with 1 mL single-dose syringe of Sterile Water for Injection, USP for reconstitution
Use as a Diagnostic Aid
10 Single-dose vials | 63323-596-13 | 1 mg per vial | 1 mL single-dose vial of Glucagon for Injection
Diagnostic Kit | 63323-593-03 | 1 mg per vial | 1 mL single-dose vial of Glucagon for Injection with 1 mL single-dose vial of Sterile Water for Injection, USP for reconstitution

16.2 Recommended Storage

Before Reconstitution

The package containing Glucagon for Injection vials may be stored up to 24 months at 20° to 25° C (68° to 77° F) [see USP Controlled Room Temperature] prior to reconstitution. Do not freeze. Keep in the original package to protect from light.

After Reconstitution

Use reconstituted glucagon solution immediately. Discard any unused portion [see Dosage and Administration (2.3)].

17 PATIENT COUNSELING INFORMATION

Advise the patient to read the FDA-approved patient labeling (Patient Information and Instructions for Use).

Recognition of Severe Hypoglycemia

Inform patient and family members or caregivers on how to recognize the signs and symptoms of severe hypoglycemia and the risks of prolonged hypoglycemia.

Administration

Review the Patient Information and Instructions for Use with the patient and family members or caregivers.

Serious Hypersensitivity

Inform patients that allergic reactions can occur with Glucagon for Injection. Advise patients to seek immediate medical attention if they experience any symptoms of serious hypersensitivity reactions [see Warnings and Precautions (5.3)].

PATIENT INFORMATION
Glucagon (GLOO-ka-gon)
for injection, for subcutaneous, intramuscular or
intravenous use

What is Glucagon?
Glucagon is a prescription medicine used:

- to treat very low blood sugar (severe hypoglycemia) in people with diabetes.
- to stop stomach movement (gastrointestinal motility inhibitor) in patients receiving radiology exams.

Who should not use Glucagon?
Do not use Glucagon if:

- you have a tumor in the gland on top of your kidneys (adrenal gland) called a pheochromocytoma.
- you have a tumor in your pancreas called an insulinoma.
- you are allergic to glucagon or lactose or any of the ingredients in Glucagon. See the end of this Patient Information leaflet for a complete list of ingredients in Glucagon.
- you have tumors in your pancreas called Glucagonomas because it could cause low blood sugar when used for your radiology exam.

What should I tell my doctor before using Glucagon?
Before using Glucagon, tell your doctor about all of your medical conditions, including if you:

- have kidney problems.
- have pancreas problems.
- have not had food or water for a long time (prolonged fasting or starvation).
- have low blood sugar that does not go away (chronic hypoglycemia).
- have heart problems.
- are pregnant or plan to become pregnant. It is not known if Glucagon will harm your unborn baby.
- are breastfeeding or plan to breastfeed. It is not known if Glucagon passes into your breast milk.

Tell your doctor about all the medicines you take, including prescription and over-the-counter medicines, vitamins and herbal supplements. Glucagon may affect the way other medicines work, and other medicines may affect how Glucagon works. Know the medicines you take. Keep a list of them to show your doctor and pharmacist when you get a new medicine.

How should I use Glucagon?

- Read the detailed Instructions for Use that come with Glucagon.
- Use Glucagon exactly as your doctor tells you to.
- Make sure that you and your family know how to use Glucagon the right way before you need it.
- Act quickly. Having very low blood sugar for a period of time may be harmful.
- Call for emergency medical help right after you use Glucagon.
- If the person does not respond after 15 minutes, another dose may be given, if available.
- Eat sugar or a sugar sweetened product such as a regular soft drink or fruit juice as soon as you are able to swallow.
- Tell your doctor each time you use Glucagon. Your doctor may need to change the dose of your diabetes medicines.

What are the possible side effects of Glucagon?
Glucagon may cause serious side effects, including:

- High blood pressure. Glucagon can cause high blood pressure in certain people with tumors in their adrenal glands.
- Low blood sugar. Glucagon can cause low blood sugar in patients with tumors in their pancreas called insulinomas and Glucagonomas by making too much insulin in their bodies.
- Serious allergic reactions. Call your doctor or get medical help right away if you have a serious allergic reaction including:
  - rash
  - difficulty breathing
  - low blood pressure
- High blood sugar. If you receive Glucagon before your radiology exam it can cause high blood sugar. Your doctor will monitor your blood sugar levels during your treatment.
- Heart problems. If you have heart problems and receive Glucagon before your radiology exam, you may have an increase in your blood pressure and pulse while using Glucagon which could be life threatening.Your doctor will monitor your heart during treatment.

The most common side effects of Glucagon include:

- swelling at the injection site
- redness at the injection site
- vomiting
- nausea

- decreased blood pressure
- weakness
- headache
- dizziness

- pale skin
- diarrhea
- sleepiness or drowsiness

Tell your doctor if you have any side effect that bothers you or that does not go away. These are not all the possible side effects of Glucagon. Call your doctor for medical advice about side effects. You may report side effects to FDA at 1-800-FDA-1088.

How should I store Glucagon?
Before you mix the Glucagon powder and liquid:

- Store Glucagon at room temperature between 68°F to 77°F (20°C to 25°C) for up to 24 months (2 years).
- Do not freeze Glucagon.
- Keep Glucagon in its original package Glucagon and out of light.

After you mix the Glucagon powder and liquid:

- Use Glucagon right away.
- Throw away any unused Glucagon.
- Glucagon should be clear and colorless. Do not use Glucagon if it is cloudy or if you see particles in the solution.

Keep Glucagon and all medicines out of the reach of children.

General information about the safe and effective use of Glucagon:
Medicines are sometimes prescribed for purposes other than those listed in a Patient Information leaflet. Do not use Glucagon for a condition for which it was not prescribed. Do not give Glucagon to other people, even if they have the same symptoms that you have. It may harm them. You can ask your pharmacist or healthcare provider for information about Glucagon that is written for health professionals.

What are the ingredients in the Glucagon?
Active Ingredient: Glucagon
Inactive ingredients: lactose monohydrate and sterile water for reconstitution
For more information, go to www.fresenius-kabi.com/us or call 1-800-551-7176.

This Patient Information has been approved by the U.S. Food and Drug Administration

Approved: 09/2019

Instructions for Use

Glucagon (GLOO-ka-gon)

for injection, for subcutaneous, intramuscular or intravenous use

Read this Instructions for Use before you start using Glucagon and each time you get a refill. There may be new information. This information does not take the place of talking with your doctor about your medical condition or treatment. Talk to your doctor or pharmacist if you have any questions about how to use Glucagon.

Important:

- Read and become familiar with this Instructions for Use before an emergency happens.
- Show your family members and others where you keep your Glucagon Emergency Kit for Low Blood Sugar and how to use it the right way.
- Call for emergency medical help right after you use Glucagon.
- Do not share your Glucagon syringes or needles with another person. You may give other people a serious infection or other people may get a serious infection from you.
- The prefilled syringe that comes with your Glucagon Emergency Kit for Low Blood Sugar is meant for use with Glucagon only. Do not use Glucagon syringes to inject other medicines.

How should I store Glucagon?

Before you mix the Glucagon powder and liquid:

- Store Glucagon at room temperature between 68° to 77°F (20° to 25°C). Check the expiration date on your vial of Glucagon. Do not use Glucagon if the expiration date has passed.
- Do not freeze Glucagon.
- Keep Glucagon in its original package and Glucagon out of light.

After you mix the Glucagon powder and liquid:

- Use Glucagon right away.
- Throw away any unused Glucagon.
- Glucagon should be clear and colorless. Do not use Glucagon if it is cloudy or if you see particles in the solution.

Supplies you will need for your Glucagon injection (See Figure A):

- 1 Glucagon Emergency Kit for Low Blood Sugar that contains:
  - 1 vial that contains 1 mg of Glucagon for injection and 1 prefilled glass syringe with attached needle that contains 1 mL of Sterile Water for Injection.

Figure A

- 1 puncture resistant container for throwing away used needles and syringes. See “How should I dispose of (throw away) used Glucagon prefilled syringes” at the end of these instructions.
- Cotton ball or gauze pad (not included in kit)
- Preparing the Glucagon dose:
- The Glucagon medicine comes as a dry powder. Before you use Glucagon, you must mix the dry powder with the syringe of sterile water that comes in the Glucagon Emergency Kit for Low Blood Sugar. Do not use any other liquid to mix the medicine.
- Check that the orange plastic cap on your vial of Glucagon is firmly attached. Do not use the vial of Glucagon if the orange plastic cap is loose or missing.

Step 1. Using your thumb, flip the orange plastic cap off the Glucagon vial (See Figure B). | Figure B
Step 2. Pick up the prefilled syringe containing sterile water. Hold the syringe with 1 hand and with your other hand pull the needle cover off the syringe (See Figure C).; - Do not remove the plastic backstop from the syringe. | Figure C
Step 3. Pick up the Glucagon vial. Hold the vial of dry powder with 1 hand and with your other hand push the needle of the prefilled syringe through the center of the rubber stopper (See Figure D). | Figure D
Step 4. Hold the vial and syringe together, with the needle still inserted into the vial. Carefully turn the vial and syringe together right side up. Slowly push the plunger down until the syringe is empty (See Figure E).; - Do not take the syringe out of the vial. | Figure E
Step 5. Hold the entire unit (the vial and syringe) in 1 hand and gently shake the vial until the powder is completely dissolved (See Figure F).; - Do not use if it is cloudy or if you see particles in the solution. - Do not take the syringe out of the vial. | Figure F
Step 6. Firmly hold the vial and syringe together, with the needle still inserted into the vial. Carefully turn the vial and syringe together upside down. Gently pull down on the plunger and slowly withdraw all of the liquid into the syringe (See Figure G).; - Do not pull the plunger out of the syringe. | Figure G
Step 7. Keep the needle inside the vial. Check the syringe for air bubbles. If you see bubbles, tap the syringe until the bubbles rise to the top of the syringe (See Figure H). Gently push on the plunger to move only the air bubbles back into the vial. | Figure H
Step 8. Hold the vial and syringe as shown (See Figure I) | Figure I
Giving the Glucagon for Injection:
Step 9. Choose the injection site (See Figure J). Common injection sites for Glucagon are upper arms, thighs, or buttocks. Patient does not need to be laying down to administer the medication as long as the common injection sites can be easily accessed. | Figure J
Step 10. With 1 hand gently pinch the skin at the injection site. With your other hand insert the needle into the skin and push the syringe plunger down until the syringe is empty (See Figure K). | Figure K
After Giving the Glucagon injection:
Step 11. Pull the needle out of the skin and press on the injection site (See Figure L). Use a gauze pad or cotton ball (not included in the kit) if needed to press the injection site to make sure there is no direct contact with the skin. | Figure L

Throw away your used syringe with the needle attached and any Glucagon you did not use. See “How should I dispose of (throw away) used Glucagon prefilled syringes” at the end of these instructions.

Step 12. Turn the person on their side. When an unconscious person awakens, they may vomit. Turning the person on their side will lessen the chance of choking.

Step 13. Call for emergency medical help right away. If the person does not respond after 15 minutes,

another dose may be given, if available.

Step 14. Feed the person as soon as they are awake and able to swallow.

Give the person a fast acting source of sugar (such as a regular soft drink or fruit juice) and a long acting source of sugar (such as crackers and cheese or a meat sandwich).

Step 15. Even if the Glucagon for Injection treatment wakes the person, tell their doctor right away. The doctor should be told whenever a severe drop in blood sugar (hypoglycemia reaction) happens. The person's dose of diabetes medicine may need to be changed.

Hypoglycemia may happen again after receiving Glucagon for Injection treatment. Early symptoms of hypoglycemia may include:

- sweating
- drowsiness
- dizziness
- sleep disturbances
- irregular heartbeat (palpitation)
- anxiety
- tremor
- blurred vision
- hunger
- slurred speech

- restlessness
- depressed mood
- tingling in the hands, feet, lips, or tongue
- irritability
- abnormal behavior
- lightheadedness
- unsteady movement
- inability to concentrate
- personality changes
- headache

If not treated early, hypoglycemia may worsen and the person may have severe hypoglycemia. Signs of severe hypoglycemia include:

- confusion
- unconsciousness

- seizures
- death

How should I dispose of (throw away) Glucagon pre-filled syringes?

- Put used syringes in a FDA-cleared sharps disposal container right away after use. Do not throw away (dispose of) loose needles and syringes in your household trash.
- If you do not have a FDA-cleared sharps disposal container, you may use a household container that is:
  - made of a heavy-duty plastic,
  - can be closed with a tight-fitting, puncture-resistant lid, without sharps being able to come out,
  - upright and stable during use,
  - leak-resistant, and
  - properly labeled to warn of hazardous waste inside the container.
- When your sharps disposal container is almost full, you will need to follow your community guidelines for the right way to dispose of your sharps disposal container. There may be state or local laws about how you should throw away used needles and syringes. For more information about safe sharps disposal, and for specific information about sharps disposal in the state that you live in, go to the FDA's website at: http://www.fda.gov/safesharpsdisposal.
- Do not dispose of your used sharps disposal container in your household trash unless your community guidelines permit this. Do not recycle your used sharps disposal container.

Keep Glucagon and all medicines out of the reach of children.

This Instructions for Use has been approved by the U.S. Food and Drug Administration. Approved: 09/2019

The brand names mentioned in this document are the trademarks of their respective owners.

Manufactured by:
Fresenius Kabi
Lake Zurich, IL 60047

www.fresenius-kabi.com/us
451541

PACKAGE LABEL

PACKAGE LABEL - PRINCIPAL DISPLAY - Glucagon 1 mg Vial Label
509813
Glucagon for Injection (Synthetic)
1 mg per vial
For subcutaneous, intramuscular or intravenous injection.
Reconstitute with Sterile Water for Injection, USP
Rx only

PACKAGE LABEL - PRINCIPAL DISPLAY - Sterile Water 1 mL Single-Dose Syringe Label
1 mL Single-Dose Syringe
Sterile Water for Injection, USP
For drug diluent use only
1 mL

PACKAGE LABEL - PRINCIPAL DISPLAY - Glucagon 1 mg Top of Clamshell
NDC 63323-582-82
Reconstitute with accompanying diluent immediately before use.

Glucagon Emergency Kit for Low Blood Sugar
Glucagon for Injection 1 mg per vial
This Kit contains:

- One single-dose vial with 1 mg of Glucagon for Injection
- One prefilled syringe with 1 mL of Sterile Water for Injection, USP (Diluent)

For subcutaneous, intramuscular or intravenous injection

Rx only